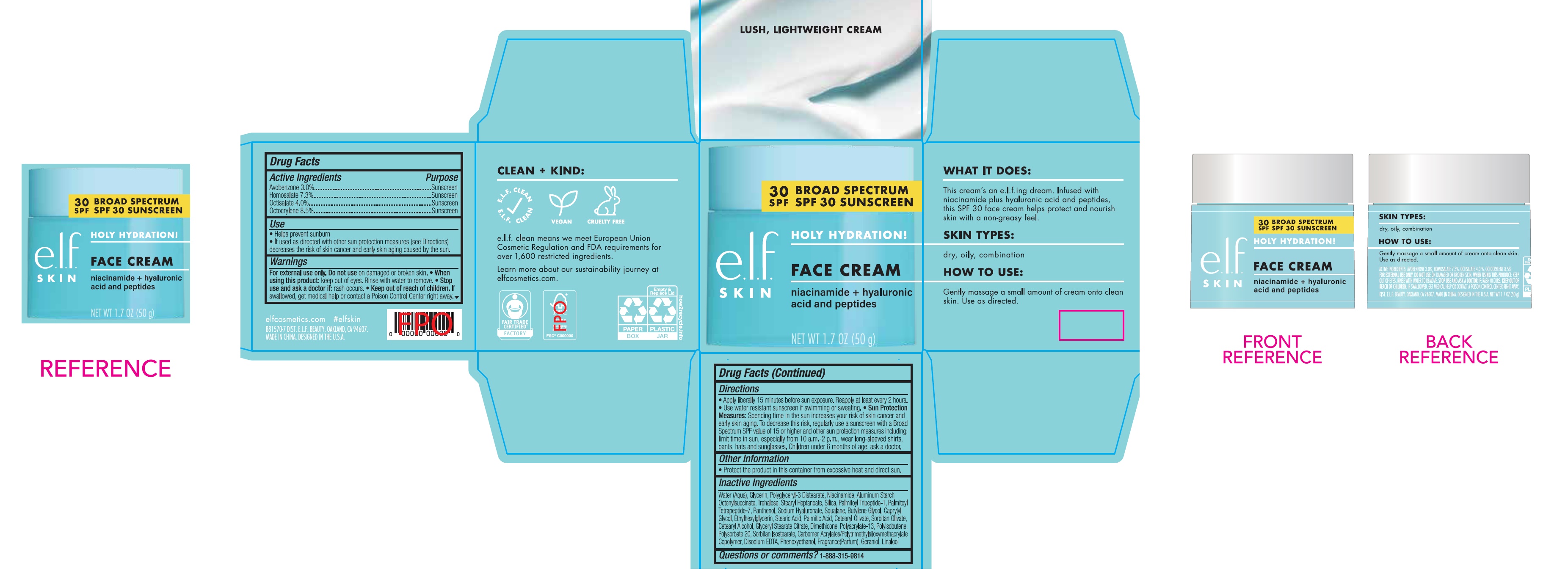 DRUG LABEL: e l f Holy Hydration Face SPF 30 Sunscreen,
NDC: 76354-447 | Form: CREAM
Manufacturer: e.l.f. Cosmetics, Inc
Category: otc | Type: HUMAN OTC DRUG LABEL
Date: 20251107

ACTIVE INGREDIENTS: AVOBENZONE 30 mg/1 g; HOMOSALATE 73 mg/1 g; OCTISALATE 40 mg/1 g; OCTOCRYLENE 85 mg/1 g
INACTIVE INGREDIENTS: WATER; GLYCERIN; POLYGLYCERYL-3 DISTEARATE; NIACINAMIDE; ALUMINUM STARCH OCTENYLSUCCINATE; TREHALOSE; STEARYL HEPTANOATE; SILICON DIOXIDE; PALMITOYL TRIPEPTIDE-1; PALMITOYL TETRAPEPTIDE-7; PANTHENOL; HYALURONATE SODIUM; SQUALANE; BUTYLENE GLYCOL; CAPRYLYL GLYCOL; ETHYLHEXYLGLYCERIN; STEARIC ACID; PALMITIC ACID; CETEARYL OLIVATE; SORBITAN OLIVATE; CETOSTEARYL ALCOHOL; GLYCERYL STEARATE CITRATE; DIMETHICONE; POLYACRYLATE-13; POLYSORBATE 20; SORBITAN ISOSTEARATE; CARBOMER HOMOPOLYMER, UNSPECIFIED TYPE; EDETATE DISODIUM; PHENOXYETHANOL; GERANIOL; LINALOOL, (+/-)-

e.l.f. Holy Hydration Face Cream SPF 30 Sunscreen,

Active Ingredients

Avobenzone 3.0%

Homosalate 7.3%

Octisalate 4.0%

Octocrylene 8.5%

Purpose

Sunscreen

Use

- Helps prevent sunburn
- If used as directed with other sun protection measures (see Directions) decreases the risk of skin cancer and early skin aging caused by the sun.

Warnings

For external use only.

Do not use

on damaged or broken skin.

When using this product:

Keep out of eyes. Rinse with water to remove.

Stop use and ask a doctor if:

rash occurs.

Keep out of reach of children.

If swallowed, get medical help or contact a Poison Control Center right away.

Other Information

- Apply liberally 15 minutes before sun exposure. Reapply at least every 2 hours.
- Use water resistant sunscreen if swimming or sweating.
- Sun Protection Measures:Spending time in the sun increases your risk of skin cancer and early skin aging. To decrease this risk, regularly use a sunscreen with a Broad Spectrum SPF value of 15 or higher and other sun protection measures including: limit time in sun, especially from 10 a.m.-2 p.m., wear long-sleeved shirts, pants, hats and sunglasses. Children under 6 months of age: ask a doctor.

Other Information

- Protect the product in this container from excessive heat and direct sun.

Inactive Ingredients

Water (Aqua), Glycerin, Polyglyceryl-3 Distearate, Niacinamide, Aluminum Starch Octenylsuccinate, Trehalose, Stearyl Heptanoate, Silica, Palmitoyl Tripeptide-1, Palmitoyl Tetrapeptide-7, Panthenol, Sodium Hyaluronate, Squalane, Butylene Glycol, Caprylyl Glycol, Ethylhexylglycerin, Stearic Acid, Palmitic Acid, Cetearyl Olivate, Sorbitan Olivate, Cetearyl Alcohol, Glyceryl Stearate Citrate, Dimethicone, Polyacrylate-13, Polyisobutene, Polysorbate 20, Sorbitan Isostearate, Carbomer, Acrylates/Polytrimethylsiloxymethacrylate Copolymer, Disodium EDTA, Phenoxyethanol, Fragrance(Parfum), Geraniol, Linalool

Questions or comments?

1-888-315-9814